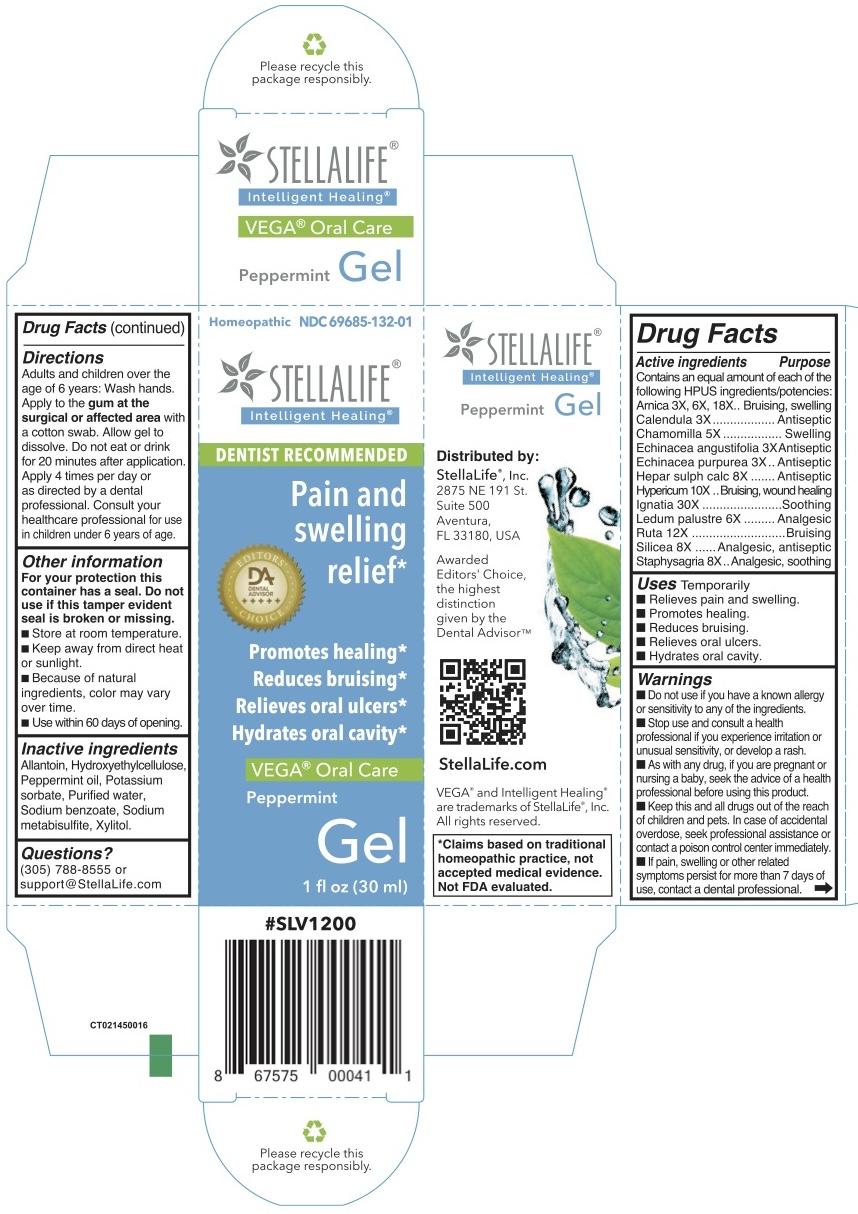 DRUG LABEL: StellaLife VEGA Oral Care Peppermint
NDC: 69685-132 | Form: GEL
Manufacturer: StellaLife, Inc.
Category: homeopathic | Type: HUMAN OTC DRUG LABEL
Date: 20251222

ACTIVE INGREDIENTS: ARNICA MONTANA 3 [hp_X]/1 mL; MATRICARIA RECUTITA 5 [hp_X]/1 mL; ECHINACEA PURPUREA 3 [hp_X]/1 mL; DELPHINIUM STAPHISAGRIA SEED 8 [hp_X]/1 mL; CALCIUM SULFIDE 8 [hp_X]/1 mL; LEDUM PALUSTRE TWIG 6 [hp_X]/1 mL; CALENDULA OFFICINALIS FLOWERING TOP 3 [hp_X]/1 mL; ECHINACEA ANGUSTIFOLIA 3 [hp_X]/1 mL; HYPERICUM PERFORATUM 10 [hp_X]/1 mL; STRYCHNOS IGNATII SEED 30 [hp_X]/1 mL; SILICON DIOXIDE 8 [hp_X]/1 mL; RUTA GRAVEOLENS FLOWERING TOP 12 [hp_X]/1 mL
INACTIVE INGREDIENTS: POTASSIUM SORBATE; SODIUM METABISULFITE; PEPPERMINT OIL; HYDROXYETHYL CELLULOSE (100 MPA.S AT 2%); WATER; SODIUM BENZOATE; XYLITOL; ALLANTOIN

Oral Care Gel - Peppermint - StellaLife VEGA

Active Ingredients

Arnica 3X, 6X, 18X, Calendula 3X, Chamomilla 5X, Echinacea angustifolia 3X, Echinacea purpurea 3X, Hepar sulph calc 8X, Hypericum 10X, lgnatia 30X, Ruta 12X, Silicea 8X, Staphysagria 8X

Purpose

Active Ingredient | Purpose
Arnica | Bruising, swelling
Calendula | Antiseptic
Chamomilla | Swelling
Echinacea angustifolia | Antiseptic
Echinacea purpurea | Antiseptic
Hepar sulph calc | Antiseptic
Hypericum | Bruising, wound healing
lgnatia | Soothing
Ledum palustre | Analgesic
Ruta | Bruising
Silicea | Analgesic, antiseptic
Staphysagria | Analgesic, soothing

Uses

Temporarily

- Relieves pain and swelling.
- Promotes healing.
- Reduces bruising.
- Relieves oral ulcers.
- Hydrates oral cavity.

Directions

Adults and children over the age of 6 years: Wash hands. Apply to the gum at the surgical or affected area with a cotton swab. Allow gel to dissolve. Do not eat or drink for 20 minutes after application. Apply 4 times per day or as directed by a dental professional. Consult your healthcare professional for use in children under6 years of age.

Keep out of reach of children

■ Keep this and all drugs out of the reach of children and pets. In case of accidental overdose, seek professional assistance or

contact a poison control center immediately

Pregnancy warning

■ As with any drug, if you are pregnant or nursing a baby, seek the advice of a health professional before using this product.

Inactive ingredients

Allantoin, Hydroxyethylcellulose, Peppermint oil, Potassium sorbate, Purified water, Sodium benzoate, Sodium metabisulfite, Xylitol.

■ Do not use if you have a known allergy or sensitivity to any of the ingredients.

Stop use

■ Stop use and consult a health professional is you experience irritation or unusual sensitivity, or develop a rash,

Warnings

For your protection this container has a seal. Do not use if this tamper evident seal is broken or missing.

Ask dential professional

■ If pain, swelling or other related symptoms persist for more than7 days of use, contact a dental professional.

Other information

■ Store at room temperature.

■ Keep away from direct heat or sunlight.

■ Because of natural ingredients. color may vary overtime.

■ Use within 60 days of opening

Questions?

(305) 788-8555 or

support@StellaLife.com